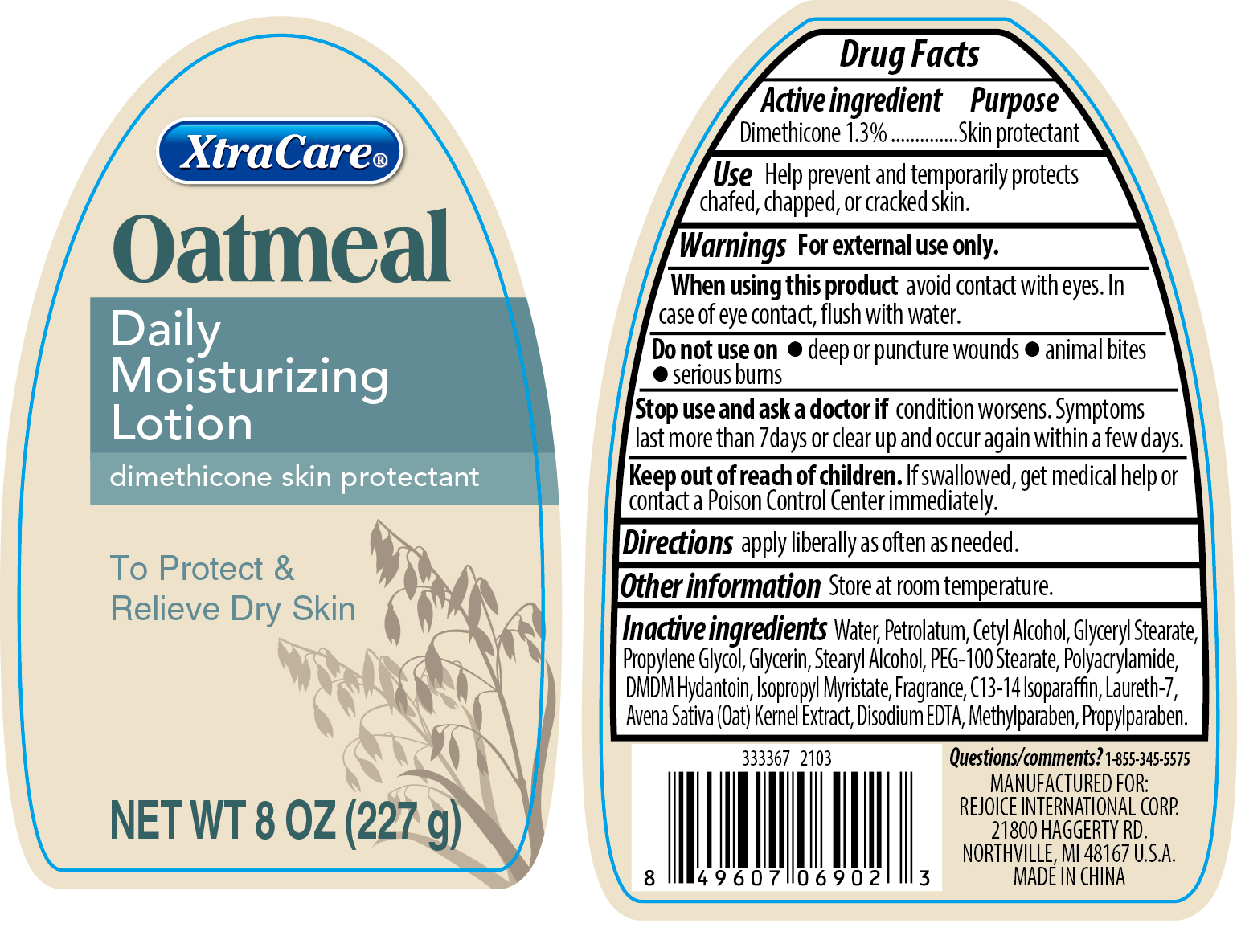 DRUG LABEL: XtraCare Oatmeal Daily Moisturizing
NDC: 57337-138 | Form: LOTION
Manufacturer: Rejoice International Inc.
Category: otc | Type: HUMAN OTC DRUG LABEL
Date: 20250213

ACTIVE INGREDIENTS: DIMETHICONE 1.3 g/100 g
INACTIVE INGREDIENTS: STEARYL ALCOHOL; METHYLPARABEN; GLYCERYL MONOSTEARATE; GLYCERIN; DMDM HYDANTOIN; PETROLATUM; OAT; PEG-100 STEARATE; WATER; EDETATE DISODIUM; PROPYLPARABEN; POLYACRYLAMIDE (10000 MW); C13-14 ISOPARAFFIN; ISOPROPYL MYRISTATE; LAURETH-7; PROPYLENE GLYCOL; CETYL ALCOHOL

XtraCare Oatmeal Daily Moisturizing Lotion 8 oz

Active ingredient

Dimethicone 1.3%

Purpose

Skin Protectant

Uses

- Help prevent and temporarily protects chafed, chapped, or cracked skin.

Warnings

For external use only

When using this product avoid contact with eyes. In case of eye contact, flush with water.

Do not use on

- deep or puncture wounds
- animal bites
- serious burns

Stop use and ask a doctor if

condition worsens. Symptoms last more than 7 days or clear up and occur again within a few days

Keep out of reach of children.

If swallowed, get medical help or contact a Poison Control Center immediately.

DOSAGE AND ADMINISTRATION

Directions apply liberally as often as needed.

Other information Store at room temperature.

INACTIVE INGREDIENT

Water, Petrolatum, Cetyl Alcohol, Glyceryl Stearate, Propylene Glycol, Glycerin, Stearyl Alcohol, PEG-100 Stearate, Polyacrylamide, DMDM Hydantoin, Isopropyl Myristate, Fragrance, C13-14 Isoparaffin, Laureth-7, Avena Sativa (Oat) Kernel Extract, Disodium, EDTA, Methylparaben, Propylparaben.

Questions/comments? 1-855-345-5575